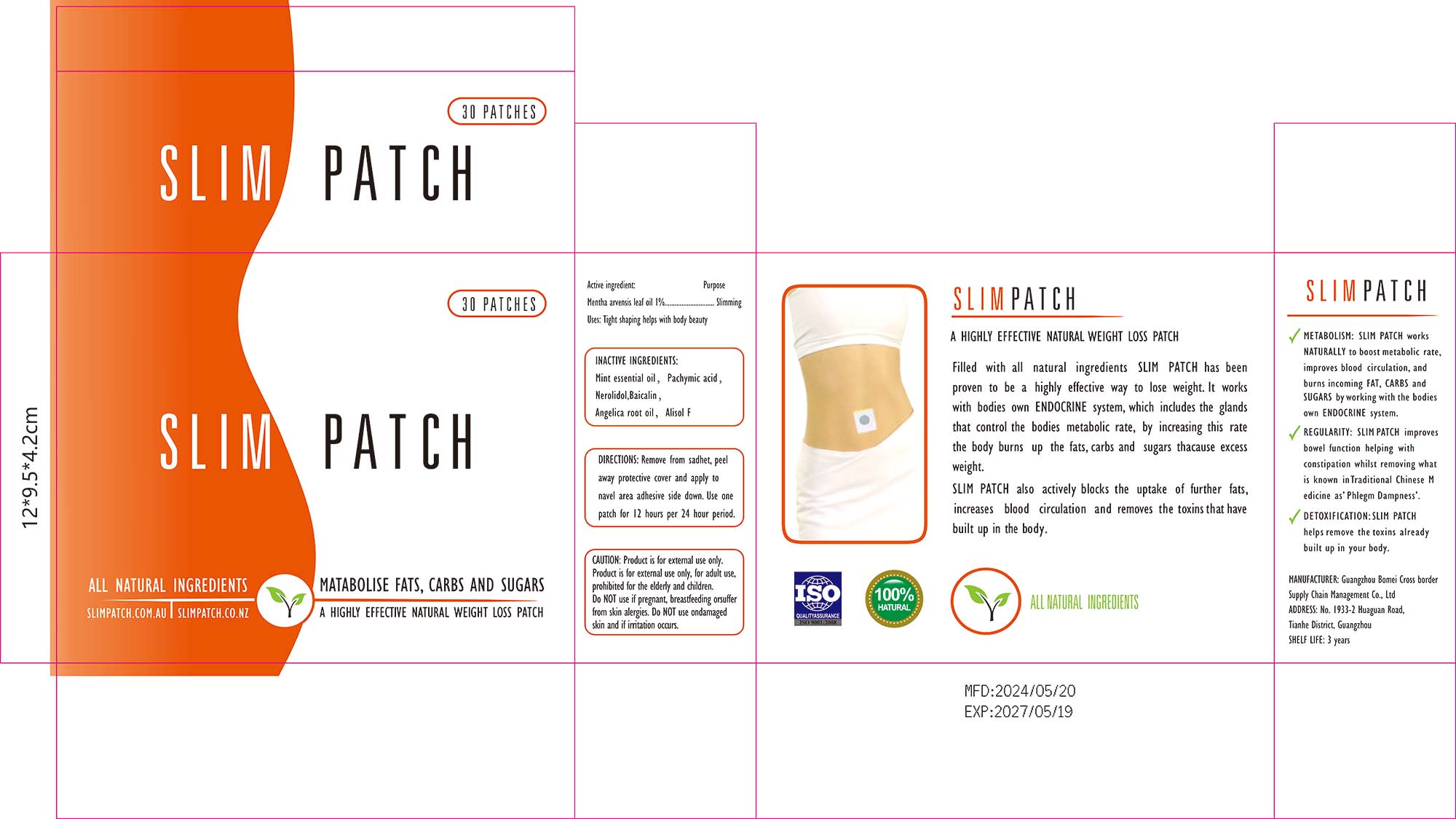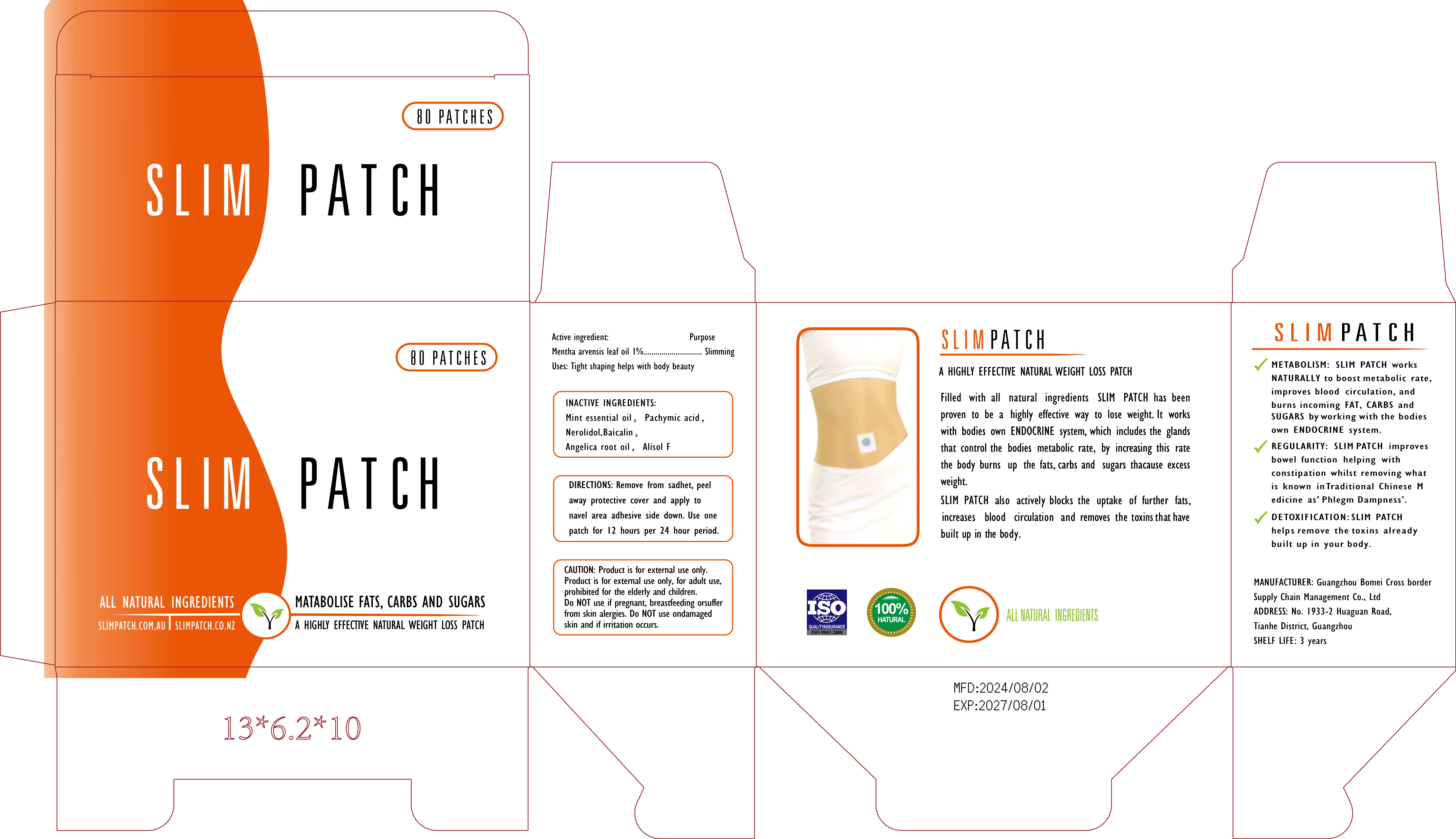 DRUG LABEL: SLIM Patch
NDC: 84537-002 | Form: PATCH
Manufacturer: Guangzhou Bomei Cross border Supply Chain Management Co., Ltd
Category: otc | Type: HUMAN OTC DRUG LABEL
Date: 20240807

ACTIVE INGREDIENTS: MENTHA ARVENSIS LEAF OIL 1 g/100 1
INACTIVE INGREDIENTS: ALISOL F; ANGELICA ROOT OIL; NEROLIDOL; BAICALIN; PACHYMIC ACID

SLIM PATCH

ACTIVE INGREDIENT

MENTHA ARVENSIS LEAF OIL 1%

PURPOSE

Slimming

KEEP OUT OF REACH OF CHILDREN SECTION

INDICATIONS AND USAGE

Uses: Tight shaping helps with body beauty

WARNINGS

Product is for external use only,Product is for external use only, for adult use,prohibited for the elderly and children.Do NOT use if pregnant, breastfeeding orsuferfrom skin alergies. Do NOT use ondamagedskin and if irritation occurs.

DOSAGE AND ADMINISTRATION

DIRECTIONS: Remove from sadhet, peel,
away protective cover and apply tonavel area adhesive side down. Use onepatch for l2 hours per 24 hour period.

STORAGE AND HANDLING

SHELF LFE: 3 years

INACTIVE INGREDIENT

PACHYMIC ACID
NEROLIDOL
BAICALIN
ANGELICA ROOT OIL
ALISOL F